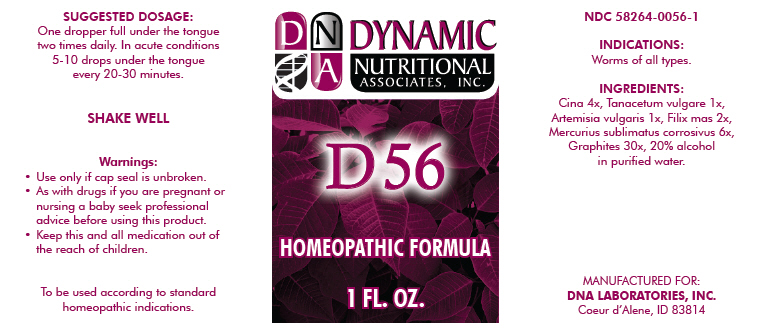 DRUG LABEL: D56
NDC: 58264-0056 | Form: SOLUTION
Manufacturer: DNA Labs, Inc.
Category: homeopathic | Type: HUMAN OTC DRUG LABEL
Date: 20250113

ACTIVE INGREDIENTS: ARTEMISIA CINA PRE-FLOWERING TOP 4 [hp_X]/1 mL; TANACETUM VULGARE WHOLE 1 [hp_X]/1 mL; ARTEMISIA VULGARIS WHOLE 1 [hp_X]/1 mL; DRYOPTERIS FILIX-MAS ROOT 2 [hp_X]/1 mL; MERCURIC CHLORIDE 6 [hp_X]/1 mL; GRAPHITE 30 [hp_X]/1 mL
INACTIVE INGREDIENTS: ALCOHOL; WATER

D-56

NDC 58264-0056-1

INDICATIONS

PURPOSE

Worms of all types.

ACTIVE INGREDIENT

INGREDIENTS

Cina 4x, Tanacetum vulgare 1x, Artemisia vulgaris 1x, Filix mas 2x, Mercurius sublimatus corrosivus 6x, Graphites 30x, 20% alcohol in purified water.

SUGGESTED DOSAGE

One dropper full under the tongue two times daily. In acute conditions 5-10 drops under the tongue every 20-30 minutes.

STORAGE AND HANDLING

SHAKE WELL

Warnings

- Use only if cap seal is unbroken.

PREGNANCY OR BREAST FEEDING

- As with drugs if you are pregnant or nursing a baby seek professional advice before using this product.

KEEP OUT OF REACH OF CHILDREN

- Keep this and all medication out of the reach of children.

To be used according to standard homeopathic indications.

PRINCIPAL DISPLAY PANEL - 1 FL. OZ. Bottle Label

DYNAMIC
NUTRITIONAL
ASSOCIATES, INC.

D 56

HOMEOPATHIC FORMULA

1 FL. OZ.